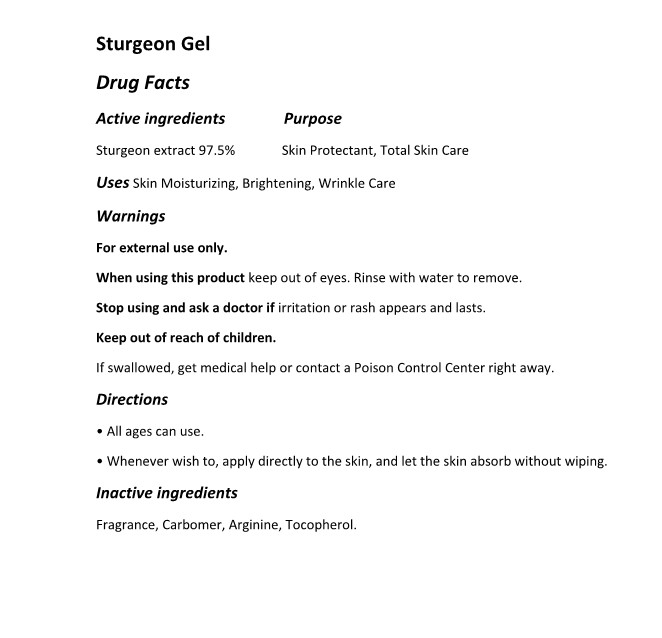 DRUG LABEL: The Zoeun Skin Sturgeon Gel
NDC: 83636-603 | Form: GEL
Manufacturer: Sturgeonbio Co.,Ltd.
Category: otc | Type: HUMAN OTC DRUG LABEL
Date: 20240115

ACTIVE INGREDIENTS: STURGEON, UNSPECIFIED 97.5 g/100 mL
INACTIVE INGREDIENTS: CARBOMER HOMOPOLYMER, UNSPECIFIED TYPE; FRAGRANCE 13576; ARGININE; TOCOPHEROL

83636-603 The Zoeun Skin Sturgeon Gel

Active Ingredients

Sturgeon extract

Purposes

Skin Protectant, Total Skin Care

Uses

Skin Moisturizing, Brightening, Wrinkle Care

Warnings

Keep out of reach of children.
If swallowed, get medical help or contact a Poison Control Center right away.

Warnings

Stop using and ask a doctor if irritation or rash appears and lasts.

Warnings

When using this product keep out of eyes. Rinse with water to remove.

Warnings

For external use only.

Directions

• All ages can use.
• Whenever wish to, apply directly to the skin, and let the skin absorb without wiping.

Inactive Ingredients

Fragrance, Carbomer, Arginine, Tocopherol.